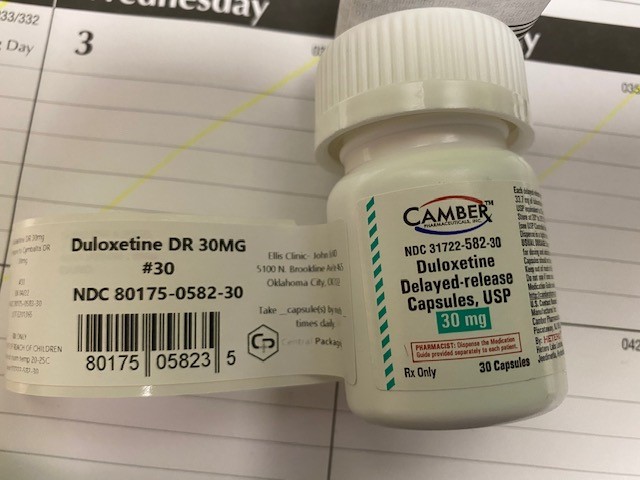 DRUG LABEL: duloxetine
NDC: 80175-0582 | Form: CAPSULE, DELAYED RELEASE
Manufacturer: Central Packaging
Category: prescription | Type: HUMAN PRESCRIPTION DRUG LABEL
Date: 20210308

ACTIVE INGREDIENTS: DULOXETINE HYDROCHLORIDE 30 mg/1 1

INDICATIONS AND USAGE

Duloxetine delayed-release capsules are indicated for the treatment of:• Major Depressive Disorder [see Clinical Studies (14.1)]• Generalized Anxiety Disorder [see Clinical Studies (14.2)]• Diabetic Peripheral Neuropathy [see Clinical Studies (14.3)]• Chronic Musculoskeletal Pain [see Clinical Studies (14.5)]

Medication Guide
Duloxetine Delayed-release Capsules
(doh-LOCKS-ah-teen)
Read this Medication Guide before you start taking duloxetine delayed-release capsules and each time you get a refill. There may be new information. This information does not take the place of talking to your healthcare provider about your medical condition or treatment.
Talk to your healthcare provider about:
• all risks and benefits of treatment with antidepressant medicines
• all treatment choices for depression or other serious mental illness
What is the most important information I should know about antidepressant medicines, depression, other serious mental illnesses, and suicidal thoughts or actions?
1. Duloxetine delayed-release capsules and other antidepressant medicines may increase suicidal thoughts or actions in some children, teenagers, or young adults within the first few months of treatment or when the dose is changed.
2. Depression and other serious mental illnesses are the most important causes of suicidal thoughts or actions. Some people may have a particularly high risk of having suicidal thoughts or actions. These include people who have (or have a family history of) bipolar illness (also called manic-depressive illness).
3. How can I watch for and try to prevent suicidal thoughts and actions?
• Pay close attention to any changes in mood, behavior, actions, thoughts, or feelings, especially sudden changes. This is very important when an antidepressant medicine is started or when the dose is changed.
• Call your healthcare provider right away to report new or sudden changes in mood, behavior, thoughts, or feelings.
• Keep all follow-up visits with your healthcare provider as scheduled. Call your healthcare provider between visits as needed, especially if you have concerns about symptoms.
Call your healthcare provider right away if you have any of the following symptoms or feelings, especially if they are new, worse, or worry you. In an emergency, call 911.
• attempts to commit suicide
• acting on dangerous impulses
• acting aggressive , being angry, or violent
• thoughts about suicide or dying
• new or worse depression
• new or worse anxiety
• panic attacks
• feeling very agitated or restless
• new or worse irritability
• trouble sleeping
• an extreme increase in activity or talking (mania)
• other unusual changes in behavior or mood
What else do I need to know about antidepressant medicines?
• Never stop an antidepressant medicine without first talking to a healthcare provider. Stopping an antidepressant medicine suddenly can cause other symptoms.
• Antidepressants are medicines used to treat depression and other illnesses. It is important to discuss all the risks of treating depression and also the risks of not treating it. Patients should discuss all treatment choices with your healthcare provider, not just the use of antidepressants.
• Antidepressant medicines have other side effects. Talk to your healthcare provider about the side effects of the medicine prescribed for you or your family member.
• Antidepressant medicines can interact with other medicines. Know all of the medicines that you or your family member takes. Keep a list of all medicines to show your healthcare provider. Do not start new medicines without first checking with your healthcare provider.
What are duloxetine delayed-release capsules?
Duloxetine delayed-release capsule is a prescription medicine used to treat certain type of depression called Major Depressive Disorder (MDD). Duloxetine delayed-release capsule belongs to a class of medicines known as SNRIs (or serotonin-norepinephrine reuptake inhibitors).
Duloxetine delayed-release capsule is also used to treat or manage:
• Generalized Anxiety Disorder (GAD)
• Diabetic Peripheral Neuropathic Pain (DPNP)
• Chronic Musculoskeletal Pain
Who should not take duloxetine delayed-release capsules?
Do Not take duloxetine delayed-release capsules if you:
• take a Monoamine Oxidase Inhibitor (MAOI). Ask your healthcare provider or pharmacist if you are not sure if you take an MAOI, including the antibiotic linezolid or intravenous methylene blue.
• Do not take an MAOI within 5 days of stopping duloxetine delayed-release capsules unless directed to do so by your healthcare provider.
• Do not start duloxetine delayed-release capsules if you stopped taking an MAOI in the last 14 days unless directed to do so by your healthcare provider.

People who take duloxetine delayed-release capsules close in time to an MAOI may have a serious problem called Serotonin Syndrome (see “What are the possible side effects of duloxetine delayed-release capsules?”).
What should I tell my healthcare provider before taking duloxetine delayed-release capsules?
Before starting duloxetine delayed-release capsules, tell your healthcare provider if you:
• have heart problems or high blood pressure
• have diabetes (Duloxetine delayed-release capsules treatment makes it harder for some people with diabetes to control their blood sugar)
• have liver problems
• have kidney problems
• have glaucoma
• have or had seizures or convulsions
• have bipolar disorder or mania
• have low sodium levels in your blood
• have delayed stomach emptying
• have or had bleeding problems
• are pregnant or plan to become pregnant. It is not known if duloxetine delayed-release capsules will harm your unborn baby. Talk to your healthcare provider about the benefits and risks of treating depression or other conditions with duloxetine delayed-release capsules during pregnancy.
• are breastfeeding or plan to breastfeed. Duloxetine can pass into your breast milk. Talk to your healthcare provider about the best way to feed your baby while taking duloxetine delayed-release capsules.
Tell your healthcare provider about all the medicines that you take, including prescription and over-the-counter medicines, vitamins, and herbal supplements. Duloxetine delayed-release capsules and some medicines may interact with each other, may not work as well, or may cause serious side effects.
Especially tell your healthcare provider if you take:
• triptans used to treat migraine headache
• medicines used to treat mood, anxiety, psychotic or thought disorders, including tricyclics, lithium, buspirone, SSRIs, SNRIs or MAOIs
• tramadol and fentanyl
• cimetidine
• the antibiotics ciprofloxacin, enoxacin
• medicine to treat irregular heart rate (like propafenone, flecainide, quinidine)
• theophylline
• the blood thinner warfarin (Coumadin, Jantoven)
• non-steroidal anti-inflammatory drug (NSAID) (like ibuprofen, naproxen or aspirin).
• over-the-counter supplements such as tryptophan or St. John’s Wort
• thioridazine (Mellaril). Mellaril together with duloxetine can cause serious heart rhythm problems or sudden death.
Ask your healthcare provider for a list of these medicines if you are not sure.
Do not take duloxetine delayed-release capsules with any other medicine that contain duloxetine.
How should I take duloxetine delayed-release capsules?
• Take duloxetine delayed-release capsules exactly as your healthcare provider tells you to take it. Your healthcare provider may need to change the dose of duloxetine delayed-release capsules until it is the right dose for you.
• Swallow duloxetine delayed-release capsules whole. Do not chew or crush duloxetine delayed-release capsules.
• Do not open the capsule and sprinkle on food or mix with liquids. Opening the capsule may affect how well duloxetine delayed-release capsule works.
• Duloxetine delayed-release capsules may be taken with or without food.
• If you miss a dose of duloxetine delayed-release capsules, take the missed dose as soon as you remember. If it is almost time for the next dose, skip the missed dose and take your next dose at the regular time. Do not take two doses of duloxetine delayed-release capsules at the same time.
• If you take too much duloxetine delayed-release capsules, call your healthcare provider or poison control center at 1-800-222-1222 right away, or get emergency treatment.
• When switching from another antidepressant to duloxetine delayed-release capsules your healthcare provider may want to lower the dose of the initial antidepressant first to potentially avoid side effects.
What should I avoid while taking duloxetine delayed-release capsules?
• Duloxetine delayed-release capsules can cause sleepiness or may affect your ability to make decisions, think clearly, or react quickly. You should not drive, operate heavy machinery, or do other dangerous activities until you know how duloxetine delayed-release capsule affects you.
• Use of duloxetine delayed-release capsules concomitantly with heavy alcohol intake may be associated with severe liver injury. Avoid heavy alcohol use while taking duloxetine delayed-release capsules.

What are the possible side effects of duloxetine delayed-release capsules?
Duloxetine delayed-release capsules may cause serious side effects, including: See “What is the most important information I should know about duloxetine delayed-release capsules?”
Common possible side effects in people who take duloxetine delayed-release capsules include:
1. liver damage. Symptoms may include:
• itching
• right upper abdominal pain
• dark urine
• yellow skin or eyes
• enlarged liver
• increased liver enzymes
2. changes in blood pressure and falls. Monitor your blood pressure before starting and throughout treatment. Duloxetine delayed-release capsules may:
• increase your blood pressure.
• decrease your blood pressure when standing and cause dizziness or fainting, mostly when first starting duloxetine delayed-release capsules or when increasing the dose.
• increase risk of falls, especially in elderly.
3. Serotonin Syndrome: This condition can be life-threatening and symptoms may include:
• agitation, hallucinations, coma or other changes in mental status
• coordination problems or muscle twitching (overactive reflexes)
• racing heartbeat, high or low blood pressure
• sweating or fever
• nausea, vomiting, or diarrhea
• muscle rigidity
• dizziness
• flushing
• tremor
• seizures
4. abnormal bleeding: Duloxetine delayed-release capsules and other antidepressant medicines may increase your risk of bleeding or bruising, especially if you take the blood thinner warfarin (Coumadin, Jantoven), a non-steroidal anti- inflammatory drug (NSAIDs, like ibuprofen or naproxen), or aspirin.

5. severe skin reactions: Duloxetine delayed-release capsules may cause serious skin reactions that may require stopping its use. This may need to be treated in a hospital and may be life-threatening. Call your health care provider right away or get emergency help if you have skin blisters, peeling rash, sores in the mouth, hives or any other allergic reactions.
6. discontinuation symptoms: Do not stop duloxetine delayed-release capsules without first talking to your healthcare provider. Stopping duloxetine delayed-release capsules too quickly or changing from another antidepressant too quickly may result in serious symptoms including:
• anxiety
• irritability
• feeling tired or problems sleeping
• headache
• sweating
• dizziness
• electric shock-like sensations
• vomiting or nausea
• diarrhea
7. manic episodes:
• greatly increased energy
• severe trouble sleeping
• racing thoughts
• reckless behavior
• unusually grand ideas
• excessive happiness or irritability
• talking more or faster than usual
8. visual problems:
• eye pain
• changes in vision
• swelling or redness in or around the eye
Only some people are at risk for these problems. You may want to undergo an eye examination to see if you are at risk and receive preventative treatment if you are.
9. seizures or convulsions
10. low salt (sodium) levels in the blood. Elderly people may be at greater risk for this. Symptoms may include:
• headache
• weakness or feeling unsteady
• confusion, problems concentrating or thinking or memory problems
11. problems with urination. Symptoms may include:
• decreased urine flow
• unable to pass any urine
The most common side effects of duloxetine delayed-release capsules include:
• nausea
• dry mouth
• sleepiness
• fatigue
• constipation
• loss of appetite
• increased sweating
• dizziness
Common possible side effects in children and adolescents who take duloxetine delayed-release capsules include:
• nausea
• decreased weight
• dizziness
Side effects in adults may also occur in children and adolescents who take duloxetine delayed-release capsules. Children and adolescents should have height and weight monitored during treatment.
Tell your healthcare provider if you have any side effect that bothers you or that does not go away.
These are not all the possible side effects of duloxetine delayed-release capsules. For more information, ask your healthcare provider or pharmacist.
Call your doctor for medical advice about side effects. You may report side effects to 1-800-FDA--1088.
How should I store duloxetine delayed-release capsules?
Store duloxetine delayed-release capsules at 20° to 25°C (68° to 77°F) [see USP Controlled Room Temperature].
Keep duloxetine delayed-release capsules and all medicines out of the reach of children.
General information about the safe and effective use of duloxetine delayed-release capsules
Medicines are sometimes prescribed for purposes other than those listed in a Medication Guide. Do not use duloxetine delayed-release capsules for a condition for which it was not prescribed. Do not give duloxetine delayed-release capsules to other people, even if they have the same symptoms that you have. It may harm them.
This Medication Guide summarizes the most important information about duloxetine delayed-release capsules. If you would like more information, talk with your healthcare provider. You may ask your healthcare provider or pharmacist for information about duloxetine delayed-release capsules that is written for healthcare professionals.
For more information, call 1-866-495-1995.
What are the ingredients in duloxetine delayed-release capsules?
Active ingredient: duloxetine hydrochloride, USP
Inactive ingredients: carboxy methyl ethyl cellulose, crospovidone, FD & C Blue 2, gelatin, hypromellose, isopropyl alcohol, polyethylene glycol, polysorbate 80, povidone, sodium lauryl sulfate, sucrose, sugar spheres, talc and titanium dioxide. In addition, the 20 mg and 60 mg capsules also contain iron oxide yellow.
The imprinting ink contains, butyl alcohol, dehydrated alcohol, isopropyl alcohol, propylene glycol, shellac, and strong ammonia solution. The 20 mg capsule also contains black iron oxide and potassium hydroxide. The 30 mg capsule also contains yellow iron oxide. The 60 mg capsule also contains potassium hydroxide and titanium dioxide.
This Medication Guide has been approved by the U.S. Food and Drug Administration
*The brands listed are trademarks of their respective owners and not trademarks of Hetero Labs Limited.
Medication Guide available at http://camberpharma.com/medication-guides

Manufactured for:

[duloxetinedraddress2]

Camber Pharmaceuticals, Inc.

Piscataway, NJ 08854

Manufactured by:

Hetero Labs Limited
Jeedimetla,
Hyderabad - 500 055, India